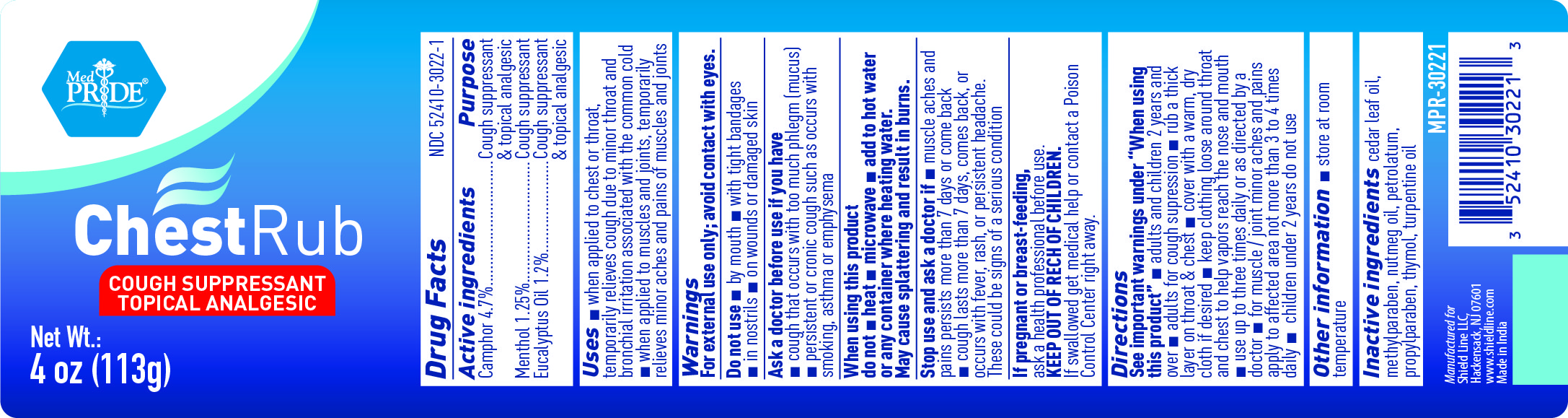 DRUG LABEL: MedPride Chest Rub
NDC: 52410-3022 | Form: OINTMENT
Manufacturer: Shield Line LLC
Category: otc | Type: HUMAN OTC DRUG LABEL
Date: 20250820

ACTIVE INGREDIENTS: CAMPHOR (SYNTHETIC) 0.047 g/1 g; EUCALYPTUS OIL 0.012 g/1 g; MENTHOL 0.0125 g/1 g
INACTIVE INGREDIENTS: CEDAR LEAF OIL; NUTMEG OIL; THYMOL; TURPENTINE OIL; PETROLATUM; METHYLPARABEN; PROPYLPARABEN

MedPride ChestRub

Drug Facts

Active ingredients

Camphor 4.7%
Menthol 1.25%

Eucalyptus oil 1.2%

Purpose

Cough suppressant & Topical Analgesic

Cough suppressant

Cough suppressant & Topical Analgesic

Uses

- when applied to chest and throat, temporarily relieves cough due to minor throat and bronchial irritation associated with the common cold
- when applied to muscles and joints, temporarily relieves minor aches and pains of muscles and joints

Warnings

For external use only; avoid contact with eyes.

Do not use

- by mouth
- with tight bandages
- in nostrils
- on wounds or damaged skin

Ask a doctor before use if you have

- cough that occurs with too much phlegm (mucus)
- persistent or chronic cough such as occurs with smoking, asthma or emphysema

When using this product, do not

- heat
- microwave
- add to hot water or any container where heating water.
  May cause splattering and result in burns.

Stop use and ask a doctor if

- muscle aches and pains persist more than 7 days or come back
- cough lasts for more than 7 days, comes back, or occurs with fever, rash, or persistent headache. A persistent cough may be a sign of a serious condition.

PREGNANCY OR BREAST FEEDING

If pregnant or breast-feeding, ask a health professional before use.

Keep out of reach of children. If swallowed, get medical help or contact a Poison Control Center right away.

Directions

see important warnings under " When using this product"

- adults and children 2 years and over
- rub a thick layer on throat & chest &
- cover with a warm, dry cloth if desired
- keep clothing loose about throat and chest to help vapors reach the nose and mouth
- use up to three times daily or as directed by doctor
- for muscle/joint minor aches and pains apply to affected area not more than 3 to 4 times daily
- children under 2 years: do not use

Other information

- store at room temperature

Inactive ingredients

cedar leaf oil, methylparaben, nutmeg oil, petrolatum, propylparaben, thymol, turpentine oil